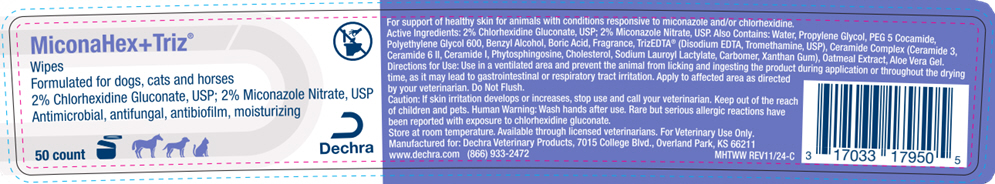 DRUG LABEL: MiconaHex plus Triz Wipes
NDC: 17033-179 | Form: CLOTH
Manufacturer: Dechra Veterinary Products
Category: animal | Type: OTC ANIMAL DRUG LABEL
Date: 20250606

ACTIVE INGREDIENTS: Chlorhexidine Gluconate 20 mg/1 1; Miconazole Nitrate 20 mg/1 1

MiconaHex + Triz® Wipes

VETERINARY INDICATIONS

For support of healthy skin for animals with conditions responsive to miconazole and/or chlorhexidine.

DESCRIPTION

Active Ingredients: 2% Chlorhexidine Gluconate, USP; 2% Miconazole Nitrate, USP.

Also Contains: Water, Propylene Glycol, PEG 5 Cocamide, Polyethylene Glycol 600, Benzyl Alcohol, Boric Acid, Fragrance, TrizEDTA® (Disodium EDTA, Tromethamine, USP), Ceramide Complex (Ceramide 3, Ceramide 6 II, Ceramide I, Phytosphingosine, Cholesterol, Sodium Lauroyl Lactylate, Carbomer, Xanthan Gum), Oatmeal Extract, Aloe Vera Gel.

DOSAGE AND ADMINISTRATION

Directions for Use: Apply to affected area as directed by your veterinarian.

PRECAUTIONS

Caution: If skin irritation develops or increases, stop use and call your veterinarian. Keep out of the reach of children and pets.

WARNINGS

Human Warning: Wash hands after use. Rare but serious allergic reactions have been reported wtth exposure to chlorhexidine gluconate.

STORAGE AND HANDLING

Store at room temperature.

Available through licensed veterinarians. For Veterinary Use Only.

Manufactured for: Dechra Veterinary Products, 7015 College Blvd., Overland Park, KS 66211
www.dechra.com (866) 933-2472

MHTWW REV09/23-C

PRINCIPAL DISPLAY PANEL - 50 Count Jar Label

MiconaHex+Triz®

Wipes
Formulated for dogs, cats and horses
2% Chlorhexidine Gluconate, USP; 2% Miconazole Nitrate, USP
Antimicrobial, antifungal, antibiofilm, moisturizing

50 count

Dechra